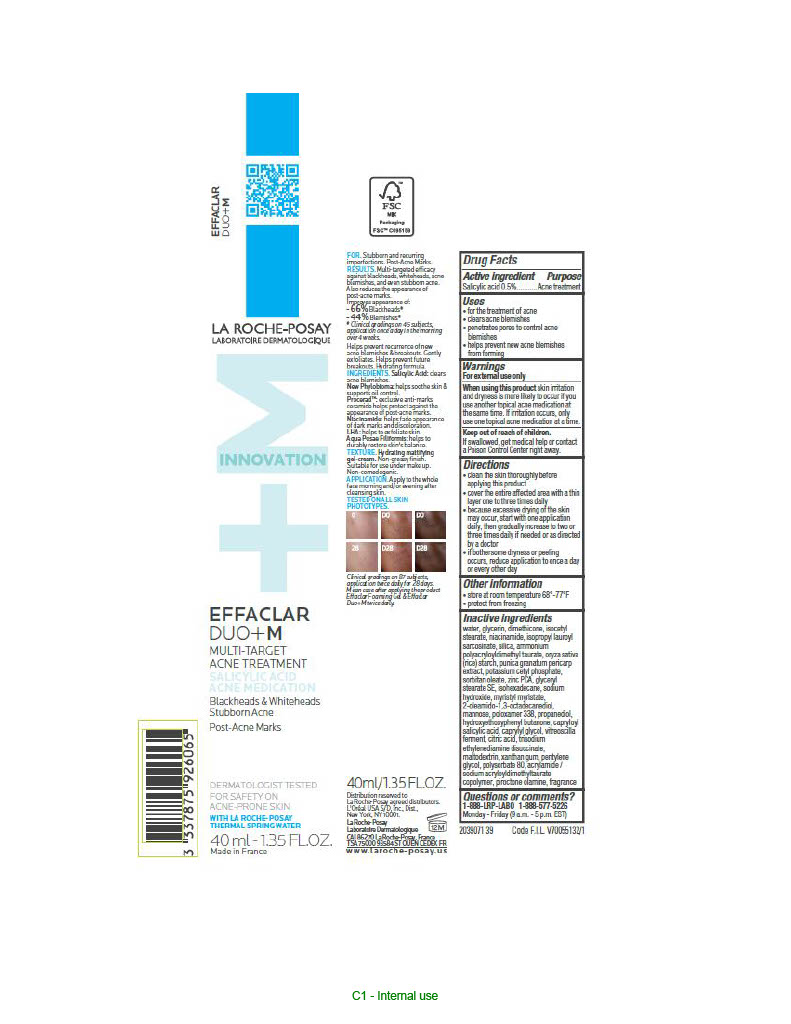 DRUG LABEL: La Roche Posay Laboratoire Dermatologique Effaclar Duo Plus M Multi Target Acne Treatment
NDC: 49967-926 | Form: LIQUID
Manufacturer: L'Oreal USA Products Inc
Category: otc | Type: HUMAN OTC DRUG LABEL
Date: 20250605

ACTIVE INGREDIENTS: SALICYLIC ACID 5 mg/1 mL
INACTIVE INGREDIENTS: WATER; GLYCERIN; DIMETHICONE; ISOCETYL STEARATE; NIACINAMIDE; ISOPROPYL LAUROYL SARCOSINATE; SILICON DIOXIDE; AMMONIUM POLYACRYLOYLDIMETHYL TAURATE; ORYZA SATIVA (RICE) STARCH; POMEGRANATE FRUIT RIND; POTASSIUM CETYL PHOSPHATE; SORBITAN OLEATE; ZINC PCA; GLYCERYL STEARATE SE; ISOHEXADECANE; SODIUM HYDROXIDE; MYRISTYL MYRISTATE; 2-OLEAMIDO-1,3-OCTADECANEDIOL; MANNOSE; POLOXAMER 338; PROPANEDIOL; HYDROXYETHOXYPHENYL BUTANONE; CAPRYLOYL SALICYLIC ACID; CAPRYLYL GLYCOL; VITREOSCILLA LYSATE; CITRIC ACID; TRISODIUM ETHYLENEDIAMINE DISUCCINATE; MALTODEXTRIN; XANTHAN GUM; PENTYLENE GLYCOL; POLYSORBATE 80; ACRYLAMIDE/SODIUM ACRYLOYLDIMETHYLTAURATE COPOLYMER (120000 MPA.S AT 1%); PIROCTONE OLAMINE

Drug Facts

Active ingredient

Salicylic acid 0.5%

Purpose

Acne treatment

Uses

- clears acne blemishes
- penetrates pores to control acne blemishes
- helps prevent new acne blemishes from forming

Warnings

For external use only

When using this product

skin irritation and dryness is more likely to occur if you use another topical acne medication at the same time. If irritation occurs, only use one topical acne medication at a time.

Keep out of reach of children.

If swallowed, get medical help or contact a Poison Control Center right away.

Directions

- clean the skin thoroughly before applying this product
- cover the entire affected area with a thin layer one to three times daily
- because excessive drying of the skin may occur, start with one application daily, then gradually increase to two or three times daily if needed or as directed by a doctor
- if bothersome dryness or peeling occurs, reduce application to once a day or every other day
- if going outside, apply sunscreen after using this product. If irritation or sensitivity develops, stop use of both products and ask a doctor.

Inactive ingredients

water, glycerin, dimethicone, isocetyl stearate, niacinamide, isopropyl lauroyl sarcosinate, silica, ammonium polyacryloyldimethyl taurate, oryza sativa (rice) starch, punica granatum pericarp extract, potassium cetyl phosphate, sorbitan oleate, zinc PCA, glyceryl stearate SE, isohexadecane, sodium hydroxide, myristyl myristate, 2-oleamido-1,3-octadecanediol, mannose, poloxamer 338, propanediol, hydroxyethoxyphenyl butanone, capryloyl salicylic acid, caprylyl glycol, vitreoscilla ferment, citric acid, trisodium ethylenediamine disuccinate, maltodextrin, xanthan gum, pentylene glycol, polysorbate 80, acrylamide/sodium acryloyldimethyltaurate copolymer, piroctone olamine, fragrance

Questions or comments?

1-888-LRP LABO

1-888-577-5226

Monday - Friday (9 a.m. - 5 p.m. EST)